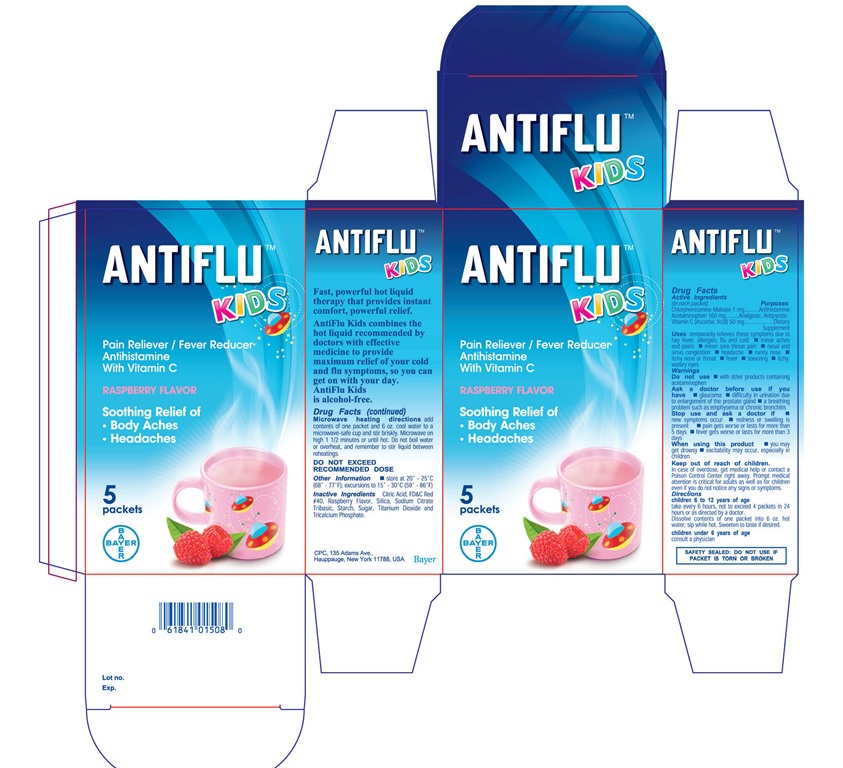 DRUG LABEL: Antiflu Kids
NDC: 0280-0046 | Form: POWDER, FOR SOLUTION
Manufacturer: Bayer HealthCare LLC
Category: otc | Type: HUMAN OTC DRUG LABEL
Date: 20250117

ACTIVE INGREDIENTS: CHLORPHENIRAMINE MALEATE 1 mg/13600 mg; ACETAMINOPHEN 160 mg/13600 mg; ASCORBIC ACID 50 mg/13600 mg
INACTIVE INGREDIENTS: CITRIC ACID MONOHYDRATE; FD&C RED NO. 40

AntiFlu-Kids